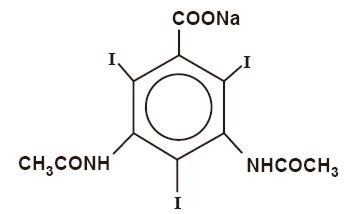 DRUG LABEL: Unknown
Manufacturer: Amersham Health Inc.
Category: prescription | Type: HUMAN PRESCRIPTION DRUG LABELING
Date: 20060413

HYPAQUE™ Sodium
(Diatrizoate Sodium Injection, USP)
50%

Sterile Aqueous Injection

For Excretory Urography
Cerebral Angiography
Peripheral Angiography
Aortography
Intraosseous Venography
Direct Cholangiography
Hysterosalpingography
Splenoportography

NOT FOR INTRATHECAL USE

Rx ONLY

DESCRIPTION

HYPAQUE sodium, brand of diatrizoate sodium, is a radiopaque diagnostic agent, water-soluble organic iodide contrast medium. In pure form, it contains 59.87 percent organically bound iodine.

The 50 percent (w/v) solution contains 300 mg iodine per mL and 0.8 mEq (18.1 mg) sodium per mL. It has an osmolality of 1515 mosm/kg (determined by VPO), and is hypertonic to blood. As a point of information only, a 10 percent solution (w/v) is isotonic. The viscosity (cp) is about 3.25 at 25° C and 2.34 at 37° C. Sodium carbonate and hydrochloric acid have been added to adjust pH between 6.5 and 7.7.The pKa is 3.4 for diatrizoic acid. If a solution of this medium is chilled, crystals may form but readily dissolve if the vial is placed in moderately hot water before use; cool to body temperature before injecting.

The sterile aqueous solution is clear and nearly colorless. It is relatively thermostable and may be autoclaved without harmful effects, although it should be protected from strong light. The 50 percent solution contains edetate calcium disodium 1:10,000 as a sequestering stabilizing agent.

Diatrizoate sodium is a triiodinated benzoic acid derivative, the sodium salt of 3,5-diacetamido-2,4,6-triiodobenzoate with a molecular weight of 635.90, and has the following structural formula:

CLINICAL PHARMACOLOGY

Intravascular injection of a radiopaque diagnostic agent opacifies those vessels in the path of the flow of the contrast medium, permitting radiographic visualization of the internal structures of the human body until significant hemodilution occurs.

At physiologic pH, the water-soluble contrast media are completely dissociated into a radiopaque anion and a solubilizing cation. While circulating in tissue fluids, the compound remains ionized. However, it is not metabolized but excreted unchanged in the urine, each diatrizoate molecule remaining "obligated" to its sodium moiety.

Following intravenous injection, the radiopaque diagnostic agents are immediately diluted in the circulating plasma. Equilibrium is reached with the extracellular compartment at about 10 minutes. Hence, the plasma concentration at 10 minutes is closely related to the dose corrected to body size.

The pharmacokinetics of the intravenously administered radiopaque contrast media are usually best described by a two compartment model with a rapid alpha phase for drug distribution and a slow beta phase for drug elimination. In patients with normal renal function, the alpha and beta half-lives were respectively 30 minutes and 120 minutes for diatrizoate. But in patients with renal functional impairment, the elimination half-life for the beta phase can be prolonged up to several days.

Injectable radiopaque diagnostic agents are excreted either through the liver or through the kidneys. These two excretory pathways are not mutually exclusive, but the main route of excretion seems to be governed by the affinity of the contrast medium for serum albumin. From 0% to 10% of diatrizoate sodium is bound to serum protein.

Diatrizoate salts are excreted unchanged predominantly through the kidneys by glomerular filtration. The amount excreted by the kidney during any period of time is determined by the filtered load; ie, the product of plasma contrast media concentration and glomerular filtration rate. The plasma concentration is dependent upon the dose administered and the body size. The glomerular filtration rate varies with the body size, sex, age, circulatory dynamics, diuretic effect of the drug, and renal function. In patients with normal renal function the maximum urinary concentration of diatrizoate sodium occurs within 10 minutes with 12 percent of the administered dose being excreted. The mean values of cumulative urinary excretion for diatrizoate sodium expressed as percentage of administered dose are 38 percent at 60 minutes, 45 percent at 3 hours, and 94 to 100 percent at 24 hours.

Urinary excretion of contrast media is delayed in infants younger than 1 month and in patients with urinary tract obstruction. The urinary iodine concentration is higher with the sodium salt of diatrizoic acid than with the meglumine salt.

The liver and small intestine provide the major alternate route of excretion for diatrizoate. In patients free of severe renal disease, the fecal recovery is less than 2 percent of the administered dose. In patients with severe renal impairment the excretion of these contrast media through the gallbladder and into the small intestine sharply increases; up to 20 percent of the administered dose has been recovered in the feces in 48 hours.

Saliva is a minor secretory pathway for injectable radiopaque diagnostic agents. In patients with normal renal function, minimal amounts of contrast media are secreted unchanged. However, in uremic patients small amounts of free iodides resulting from deiodination prior to administration or in vivo, have been detected in the saliva.

Diatrizoate salts cross the placental barrier in humans by simple diffusion and appear to enter fetal tissue passively. No apparent harm to the fetus was observed when diatrizoate sodium and diatrizoate meglumine were injected intravenously 24 hours prior to delivery. However, abnormal neonatal opacification of the small intestine and colon were detected 4 to 6 days after delivery. Procedures including radiation involve a certain risk related to the exposure of the fetus. (See PRECAUTIONS—General, Pregnancy Category C.)

Injectable radiopaque diagnostic agents are excreted unchanged in human milk. (See PRECAUTIONS—General, Nursing Mothers.)

Computerized Tomography

HYPAQUE sodium 50 percent can be administered as an intravenous bolus for brain tissue enhancement using computerized tomography. Increased tissue contrast differential for the scan is achieved either because of increased vascular (arterial, venous, or capillary bed) contrast or by blood brain barrier penetration of the medium (or its absence) in certain localized areas of disrupted vascular permeability. The degree of tissue enhancement caused by increased blood contrast is directly related to blood iodine content. However, the degree of enhancement due to extravascular accumulation of iodine resulting from blood brain barrier disruption will depend on the extent of disruption, the blood level of iodine, and the time delay prior to scanning. The nature of the pathology will determine whether an immediate or delayed scan is optimal.

Effects of Steroid Therapy

The anti-inflammatory and antiedema effects in patients receiving steroid therapy have interfered with the expected distribution of CT tissue enhancement on the scan in certain diseases.

INDICATIONS AND USAGE

HYPAQUE sodium 50 percent is indicated for excretory urography, cerebral and peripheral angiography, aortography, intraosseous venography, direct cholangiography, hysterosalpingography, splenoportography, and contrast enhancement of computed tomographic head imaging.

UROGRAPHY

Diatrizoate salts are used in small, medium, and large dose urography (see Dosage and Administration—EXCRETORY UROGRAPHY). Visualization of the urinary tract can be achieved by either direct intravenous bolus injection, intravenous drip infusion, or incidentally following intra-arterial procedures.Visualization of the urinary tract is delayed in infants less than 1 month old, and in patients with urinary tract obstruction (see CLINICAL PHARMACOLOGY).

CONTRAST ENHANCEMENT OF COMPUTED TOMOGRAPHIC HEAD IMAGING

Injectable radiopaque contrast media may be used to refine diagnostic precision in areas of the brain which may not otherwise have been satisfactorily visualized.

Tumors

Radiopaque diagnostic agents may be useful to investigate the presence and extent of certain malignancies such as: gliomas including malignant gliomas, glioblastomas, astrocytomas, oligodendrogliomas and gangliomas, ependymomas, medulloblastomas, meningiomas, neuromas, pinealomas, pituitary adenomas, craniopharyngiomas, germinomas, and metastatic lesions.

The usefulness of contrast enhancement for the investigation of the retrobulbar space and in cases of low grade or infiltrative glioma has not been demonstrated.

In calcified lesions, there is less likelihood of enhancement. Following therapy, tumors may show decreased or no enhancement.

The opacification of the inferior vermis following contrast media administration has resulted in false-positive diagnosis in a number of normal studies.

Nonneoplastic Conditions

The use of injectable radiopaque diagnostic agents may be beneficial in the image enhancement of nonneoplastic lesions. Cerebral infarctions of recent onset may be better visualized with contrast enhancement, while some infarctions are obscured if contrast media are used. The use of iodinated contrast media results in contrast enhancement in about 60 percent of cerebral infarctions studied from one to four weeks from the onset of symptoms.

Sites of active infection may also be enhanced following contrast media administration.

Arteriovenous malformations and aneurysms will show contrast enhancement. For these vascular lesions, the enhancement is probably dependent on the iodine content of the circulating blood pool.

Hematomas and intraparenchymal bleeders seldom demonstrate any contrast enhancement. However, in cases of intraparenchymal clot, for which there is no obvious clinical explanation, contrast media administration may be helpful in ruling out the possibility of associated arteriovenous malformation.

ANGIOGRAPHY

Diatrizoate salts are used for radiographic studies throughout the cardiovascular system.

Intravascular radiopaque diagnostic agents of high concentration are not recommended for cerebral or spinal angiography (see CONTRAINDICATIONS—General), and contrast agents with the lowest compatible viscosity and higher concentration of iodine (310 mg/mL to 480 mg/mL of bound iodine) must be used for angiocardiography. Contrast media approaching serum ionic content and osmolality have less potential for deleterious effects on the myocardium (see PRECAUTIONS—General, Drug Interactions).

Addition of chelating agents may contribute to toxicity in coronary angiography, and the sodium content of angiographic agents used in coronary arteriography is of crucial importance.

In addition to the following general CONTRAINDICATIONS, WARNINGS, PRECAUTIONS, and ADVERSE REACTIONS, there are additional listings in these categories under the particular procedures.

CONTRAINDICATIONS—General

HYPAQUE sodium 50 percent has no absolute contraindications in its recommended uses (see general WARNINGS and PRECAUTIONS).

Do not use HYPAQUE sodium 50 percent for myelography or for examination of dorsal cysts or sinuses which might communicate with the subarachnoid space. Even a small amount in the subarachnoid space may produce convulsions and result in fatality. (See also AORTOGRAPHY, Warnings.) Epidural injection is also contraindicated.

Urography and large dose vascular procedures are contraindicated in dehydrated azotemic patients. (See also PRECAUTIONS—General.)

WARNINGS—General

SEVERE ADVERSE EVENTS—INADVERTENT INTRATHECAL ADMINISTRATION

Serious adverse reactions have been reported due to the inadvertent intrathecal administration of iodinated contrast media that are not indicated for intrathecal use. These serious adverse reactions include: death, convulsions, cerebral hemorrhage, come, paralysis, arachnoiditis, acute renal failure, cardiac arrest, seizures, rhabdomyolysis, hyperthermia, and brain edema. Special attention must be given to insure that this drug product is not administered intrathecally.

Ionic iodinated contrast media inhibit blood coagulation, in vitro, more than nonionic contrast media. Nonetheless, it is prudent to avoid prolonged contact of blood with syringes containing ionic contrast media.

Serious, rarely fatal, thromboembolic events causing myocardial infarction and stroke have been reported during angiographic procedures with both ionic and nonionic contrast media. Therefore, meticulous intravascular administration technique is necessary, particularly during angiographic procedures, to minimize thromboembolic events. Numerous factors, including length of procedure, catheter and syringe material, underlying disease state and concomitant medications may contribute to the development of thromboembolic events. For these reasons, meticulous angiographic techniques are recommended including close attention to guidewire and catheter manipulation, use of manifold systems and/or three-way stopcocks, frequent catheter flushing with heparinized saline solutions and minimizing the length of the procedure. The use of plastic syringes in place of glass syringes has been reported to decrease but not eliminate the likelihood of in vitro clotting.

Excretory urography is potentially hazardous in patients with multiple myeloma. In some of those patients, therapeutically resistant anuria resulting in progressive uremia, renal failure, and eventually death has followed this procedure. Although neither the contrast agent nor dehydration has been proved separately to be the cause of anuria in myelomatous patients, it has been speculated that the combination of both may be causative. The risk of excretory urography in myelomatous patients is not a contraindication to the procedure; however, they require special precautions. Partial dehydration in the preparation of these patients for the examination is not recommended since this may predispose to the precipitation of myeloma protein in the renal tubules. Myeloma, which occurs most commonly in persons over age 40, should be considered before instituting urographic procedures.

Contrast media may promote sickling in individuals who are homozygous for sickle cell disease when the material is injected intravenously or intra-arterially.

Administration of radiopaque materials to patients known or suspected of having pheochromocytoma should be performed with extreme caution. If, in the opinion of the physician, the possible benefits of such procedures outweigh the considered risks, the procedures may be performed; however, the amount of radiopaque medium injected should be kept to an absolute minimum. The blood pressure should be assessed throughout the procedure and measures for treatment of a hypertensive crisis should be available.

Recent reports of thyroid storm occurring following the intravascular use of iodinated radiopaque diagnostic agents in patients with hyperthyroidism or with an autonomously functioning thyroid nodule suggest that this additional risk be evaluated in such patients before use of HYPAQUE sodium.

Contrast media administered for cardiac catheterization and angiocardiography may cause cellular injury to circulating lymphocytes. Chromosomal damage in humans includes inhibition of mitosis, increases in the number of micronuclei, and chromosome aberrations. The damages appear to be related to the contrast medium itself rather than to the x-ray radiation. It is to be noted that those agents have not been adequately tested in animal or laboratory systems.

Urography should be performed with caution in patients with severely impaired renal function and patients with combined renal and hepatic disease.

Subcutaneous extravasation, chiefly because of hypertonic cellulitis, causes transitory stinging. If the volume extravasated is small, ill effects are very unlikely. However, if the extravasation is extensive especially in poorly vascularized areas (eg, dorsum of the foot or hand), and especially in the presence of vascular disease, skin slough may occur. Injection of sterile water to dilute or addition of spreading agents to speed absorption have not been successful and may aggravate the condition.

Selective spinal arteriography or arteriography of trunks providing spinal branches can cause mild to severe muscle spasm. However, serious neurologic sequelae, including permanent paralysis, have occasionally been reported. (See also ANGIOGRAPHY, Precaution.)

In patients with subarachnoid hemorrhage, a rare association between contrast administration and clinical deterioration, including convulsions and death, has been reported. Therefore, administration of intravascular iodinated ionic contrast media in these patients should be undertaken with caution.

PRECAUTIONS—General

Diagnostic procedures which involve the use of radiopaque diagnostic agents should be carried out under the direction of personnel with the prerequisite training and with a thorough knowledge of the particular procedure to be performed. Appropriate facilities should be available for coping with any complication of the procedure, as well as for emergency treatment of severe reactions to the contrast agent itself. After parenteral administration of a radiopaque agent, competent personnel and emergency facilities should be available for at least 30 to 60 minutes since severe delayed reactions have occurred (see ADVERSE REACTIONS—General).

The possibility of a reaction, including serious, life-threatening, fatal, anaphylactic or cardiovascular reactions should always be considered (see ADVERSE REACTIONS). It is of utmost importance that a course of action be carefully planned in advance for immediate treatment of serious reactions, and that adequate and appropriate personnel be readily available in case of any reaction.

Preparatory dehydration for angiography and CT procedures is unnecessary and may be dangerous, contributing to acute renal failure in infants, young children, the elderly, patients with preexisting renal insufficiency, patients with advanced vascular disease, and diabetic patients. Dehydration in these patients seems to be enhanced by the osmotic diuretic action of urographic agents. Overnight fluid restriction for urography may be undesirable and is considered unnecessary when using this relatively high (50%) concentration.

Although azotemia is not a contraindication, the medium should be used with great care in patients with advanced renal destruction associated with severe uremia. (See also EXCRETORY UROGRAPHY, Precautions.)

Acute renal failure has been reported in diabetic patients with diabetic nephropathy and in susceptible nondiabetic patients (often elderly with preexisting renal disease) following excretory urography. Therefore, careful consideration of the potential risks should be given before performing this radiographic procedure in these patients. (See also EXCRETORY UROGRAPHY, Precautions—Preparatory Dehydration.)

Immediately following surgery, excretory urography should be used with caution in renal transplant recipients.

The possibility of an idiosyncratic reaction in susceptible patients should always be considered (see ADVERSE REACTIONS—General). The susceptible population includes patients with a history of a previous reaction to a contrast media, patients with a known sensitivity to iodine per se, and patients with a known clinical hypersensitivity: bronchial asthma, hay fever, and food allergies.

The occurrence of severe idiosyncratic reactions has prompted the use of several pretesting methods. However, pretesting cannot be relied upon to predict severe reactions and may itself be hazardous for the patient. It is suggested that a thorough medical history with emphasis on allergy and hypersensitivity, prior to injection of any contrast media, may be more accurate than pretesting in predicting potential adverse reactions.

A positive history of allergies or hypersensitivity does not arbitrarily contraindicate the use of a contrast agent, where a diagnostic procedure is thought essential, but caution should be exercised (see ADVERSE REACTIONS—General). Premedication with antihistamines or corticosteroids to avoid or minimize possible allergic reactions in such patients should be considered. Recent reports indicate that such pretreatment does not prevent serious life-threatening reactions, but may reduce both their incidence and severity.

Due to the transitory increase in the circulatory osmotic load, injections of urographic agents should be used with caution in patients with congestive heart failure. Such patients should be observed for several hours following the procedure to detect delayed hemodynamic disturbances.

General anesthesia may be indicated in the performance of some procedures in young or uncooperative children and in selected adult patients; however, a higher incidence of adverse reactions has been reported in these patients, and may be attributable to the inability of the patient to identify untoward symptoms, or to the hypotensive effect of anesthesia which can reduce cardiac output and increase the duration of exposure to the contrast agent.

Seizure activity is rare (about 0.01%) on intravenous injection of ionic contrast media. However, in the higher doses used for CT in patients with brain metastases the incidence can be much higher (1% to 10%). In these patients prophylactic use of a small parenteral dose of a diazepam is suggested immediately before injection when extra high dose CT regimens are employed.

In addition to the general precautions already described, excretory urography, angiography, and other uses also have hazards associated with the particular techniques employed. (See INDIVIDUAL INDICATIONS AND USAGE section.)

INFORMATION FOR PATIENTS

Patients receiving injectable radiopaque diagnostic agents should be instructed to:

1. Inform the physician if they are pregnant (see CLINICAL PHARMACOLOGY).
2. Inform the physician if they are diabetic or if they have multiple myeloma, pheochromocytoma, homozygous sickle cell disease or known thyroid disorder (see WARNINGS—General).
3. Inform the physician if they are allergic to any drugs, food, or if they have had any reactions to previous injections of dyes used for x-ray procedures (see PRECAUTIONS—General).
4. Inform the physician about any other medications they are currently taking, including nonprescription drugs, before they are administered this drug.

DRUG INTERACTIONS

Renal toxicity has been reported in a few patients with liver dysfunction who were given oral cholecystographic agents followed by urographic agents. Administration of intravascular urographic agents should therefore be postponed in any patient with a known or suspected hepatic or biliary disorder who has recently received a cholecystographic contrast agent.

Addition of an inotropic agent to contrast agents may produce a paradoxical depressant response which can be deleterious to the ischemic myocardium.

Diphenhydramine hydrochloride may cause precipitation when mixed in the same syringe with HYPAQUE sodium 50%.

Under certain circumstances (pH, temperature, concentrations, time), diatrizoate solutions are incompatible with promethazine hydrochloride, diphenhydramine hydrochloride, brompheniramine maleate, or papaverine hydrochloride solutions.

Do not prefill plastic syringes with HYPAQUE sodium 50% for prolonged periods (ie, for several hours or longer) before use.

DRUG/LABORATORY TEST INTERACTIONS

If any of these studies, which might be affected by contrast media are indicated, it is recommended that they be performed prior to administration of the contrast medium or two or more days afterwards.

Diatrizoate salts interfere with several laboratory urine and blood tests.

BLOOD TESTS

Coagulation: Diatrizoate salts significantly inhibit all stages of coagulation. The fibrinogen concentration, Factors V, VII, and VIII are decreased. Prothrombin time and thromboplastin time are increased.

Platelet aggregation: High levels of plasma diatrizoates inhibit platelet aggregation.

Serum calcium: Diatrizoate salts may decrease serum calcium levels. However, this depletion of serum calcium may also be the result of the addition of chelating agents (edetate disodium) in the preparation of certain contrast media.

Red cell counts: Transitory decreases in red cell counts. Technetium-99m—RBC labeling interference.

Leukocyte counts: Decrease.

Urea nitrogen (BUN): Transitory increase (see CLINICAL PHARMACOLOGY).

Serum creatinine: Transitory increase.

URINE TESTS

Contrast media which are excreted in the urine, may interfere with some laboratory determinations eg, proteinuria, specific gravity, osmolality, or bacterial cultures.

THYROID FUNCTION TESTS

Protein-bound iodine (PBI) and total serum organic iodine: Transient increase of both tests following urography have been noticed. The results of PBI and radioactive iodine uptake studies which depend on iodine estimations will not accurately reflect thyroid function for up to 16 days following administration of iodinated urographic media. However, thyroid function tests not depending on iodine estimations, eg, T3 resin uptake or free thyroxine assays are not affected.

CARCINOGENESIS, MUTAGENESIS, IMPAIRMENT OF FERTILITY

Long-term studies in animals have not been performed in order to evaluate carcinogenic potential, mutagenesis, or whether HYPAQUE sodium 50 percent can affect fertility in males or females.

PREGNANCY CATEGORY C

Animal reproduction studies have not been conducted with HYPAQUE sodium 50 percent. It is also not known whether HYPAQUE sodium 50 percent can cause fetal harm when administered to a pregnant woman or can affect reproduction capacity. HYPAQUE sodium 50 percent should be given to a pregnant woman only if clearly needed.

LABOR AND DELIVERY

It is not known whether use of these contrast agents during labor or delivery has immediate or delayed adverse effects on the fetus, prolongs the duration of labor or increases the likelihood that forceps delivery or other obstetrical intervention or resuscitation of the newborn will be necessary.

NURSING MOTHERS

Diatrizoate salts are excreted unchanged in human milk. Because of the potential adverse reactions, although it has not been established that serious adverse reactions occur in nursing infants, caution should be exercised when these contrast media are administered to a nursing woman.

PEDIATRIC USE

Infants and small children should not have any fluid restriction prior to excretory urography or any other procedures (see PRECAUTIONS—General). Guidelines for pediatric dosages are presented in DOSAGE AND ADMINISTRATION—General.

ADVERSE REACTIONS—General

Approximately 95 percent of adverse reactions accompanying the intravascular use of diatrizoate salts are of mild to moderate severity. However, life-threatening reactions and fatalities, mostly of cardiovascular origin, have occurred.

Adverse reactions to injectable contrast media fall into two categories: chemotoxic reactions and idiosyncratic reactions.

Chemotoxic reactions result from the physicochemical properties of the contrast media, the dose, and the speed of injection. All hemodynamic disturbances and injuries to organs or vessels perfused by the contrast medium are included in this category.

Idiosyncratic reactions include all other reactions. They occur more frequently in patients 20 to 40 years old. Idiosyncratic reactions may or may not be dependent on the amount of dose injected, the speed of injection, the mode of injection, and the radiographic procedure. Idiosyncratic reactions are subdivided into minor, intermediate, and severe. The minor reactions are self-limited and of short duration; the severe reactions are life-threatening and treatment is urgent and mandatory.

The reported incidence of adverse reactions to contrast media in patients with a history of allergy are twice that of the general population. Patients with a history of previous reactions to a contrast medium are three times more susceptible than other patients. However, sensitivity to contrast media does not appear to increase with repeated examinations.

Most adverse reactions to injectable contrast media appear within one to three minutes after the start of injection, but delayed reactions may occur.

Adverse reactions are grouped by organ system and listed below by decreasing order of occurrence and with an approximate incidence of occurrence. Significantly more severe reactions are listed before the other reactions regardless of frequency.

GREATER THAN 1 IN 100 PATIENTS

Body as a Whole: Reported incidences of death range from 6.6 per 1 million (0.00066 percent) to 1 in 10,000 patients (0.01 percent). Most deaths occur during injection or 5 to 10 minutes later, the main feature being cardiac arrest with cardiovascular disease as the main aggravating factor. Isolated reports of hypotensive collapse and shock following urography are found in the literature. The incidence of shock is estimated to occur in 1 out of 20,000 (0.005 percent) patients.

Cardiovascular System: The most frequent adverse reaction to diatrizoate salts is vasodilation (feeling of warmth). The estimated incidence is 49 percent.
Digestive System: Nausea 6 percent, vomiting 3 percent.
Nervous System: Paresthesia 6 percent, dizziness 5 percent.
Respiratory System: Rhinitis 1 percent, increased cough 2 percent.
Skin and Appendages: Urticaria 1 percent.
Pain at the injection site is estimated to occur in about 12 percent of the patients undergoing urography. Pain is usually due to extravasation.
Painful hot erythematous swelling above the venipuncture site was estimated to occur in more than one percent of the patients undergoing phlebography.
Special Senses: Perversion of taste 11 percent.
Urogenital System: Osmotic nephrosis of the proximal tubular cells is estimated to occur in 23 percent of patients following excretory urography.

LESS THAN 1 IN 100 PATIENTS

Other infrequently reported reactions without accompanying incidence rates are listed below, grouped by organ system.

Body as a Whole: Malaria relapse, uremia high creatinine and BUN (see PRECAUTIONS—General, Drug/Laboratory Test Interactions), thrombocytopenia, leukopenia, and anemia.
Cardiovascular System: Cerebral hematomas, hemodynamic disturbances, sinus bradycardia, transient electrocardiographic abnormalities, ventricular fibrillation, petechiae, chest pain, cardiac arrest, tachycardia, hypertension, hypotension, and vascular collapse.
Digestive System: Severe unilateral or bilateral swelling of the parotid and submaxillary glands.
Nervous System: Convulsions, paralysis, coma, memory loss. (See PRECAUTIONS—General.)
Respiratory System: Asthma, dyspnea, laryngeal edema, pulmonary edema, and bronchospasm.
Skin and Appendages: Extravasation necrosis, urticaria with or without pruritus, mucocutaneous edema, and angioneurotic edema.
Special Senses: Bilateral ocular irritation, lacrimation, itching, conjunctival chemosis, infection, and conjunctivitis.
Urogenital: Renal failure, pain.

OVERDOSAGE

At dosage levels of diatrizoate sodium above a level containing 45 g of iodine, the incidence of unpleasant side effects increases. At total dosage equivalent to 80 gI or 90 gI administered over a short period of time (eg, 30 minutes), clinical signs of systemic intolerance appear (mostly related to hyperosmolar effects) and are manifest as tremors, irritability, and tachycardia. Above these maximal tolerated dosage levels in otherwise healthy adults, an increasing incidence and severity of dyspnea and pulmonary edema should be expected.

Four cases of overdosage in infants, during urography, are reported. Three of the infants died within 19 hours of the injection. The overdose ranged from slightly above the recommended pediatric dosage to a dose exceeding 19 g/kg. The symptoms of overdosage appeared between 10 minutes to several hours after injection of the contrast medium. Adverse effects were life-threatening, affecting mainly the pulmonary and cardiovascular systems. The symptoms included: cyanosis, bradycardia, acidosis, pulmonary hemorrhage, convulsions, coma, and cardiac arrest. All infants showed a poor visualization of the kidneys and a diffuse opacification of all the tissues and vasculature. Autopsy findings showed acute pulmonary damage and/or edema of subcutaneous tissues. Treatment of an overdose of injectable radiopaque contrast media is directed toward the support of all vital functions, and prompt institution of symptomatic therapy.

The acute intravenous LD50 of diatrizoate sodium in mice is equivalent in iodine content of 5.3 gI/kg to 8.0 gI/kg and seem to be directly proportional to the rate of injection.

Diatrizoate sodium is dialyzable.

DOSAGE AND ADMINISTRATION—General

Preparation of the patient will vary with preference of the radiologist and the type of radiological procedure performed. Specific radiologic procedures used will depend on the state of the patient and the diagnostic indications. Individual doses should be tailored according to age, body size, and indication for examination. (See INDIVIDUAL INDICATIONS AND USAGE section for specific Dosage and Administration.)

Solutions of radiopaque diagnostic agents for intravascular use should be at body temperature when injected and may need to be warmed before use. In the event that crystallization occurs, the solution may be clarified by placing the vial in a water bath at 40 ° C to 5O ° C and shaking gently for two to three minutes or until the solids redissolve. If particles still persist, do not use this vial but discard it. The solution should be protected from light and any unused portion remaining in the container should be discarded.

Dilution and withdrawal of the, contrast agents should be accomplished under aseptic conditions with sterile syringes.

Parenteral drug products should be inspected visually for particulate matter and discoloration prior to administration. Avoid contaminating catheters, syringes, needles, and contrast media with glove powder or cotton fibers.

PEDIATRIC DOSAGE

Pediatric doses of injectable radiopaque diagnostic agents are generally determined on a weight basis and should be calculated for each patient individually. (See INDIVIDUAL INDICATIONS AND USAGE section.)

DRUG INCOMPATIBILITIES

Diatrizoate salts are incompatible in vitro with some antihistamines and many other drugs. It is believed that one of the chief causes of in vitro incompatibility is an alteration of pH. Turbidity of solutions of intravascular contrast medium occurs between pH 2.5 and 4.1. Another cause is chemical interaction; therefore, other pharmaceuticals should not be mixed with contrast agents in the same syringe.

INDIVIDUAL INDICATIONS AND USAGE

THE FOLLOWING SECTIONS FOR INDIVIDUAL INDICATIONS AND USAGE CONTAIN CONTRAINDICATIONS, WARNINGS, PRECAUTIONS, ADVERSE REACTIONS, AND DOSAGE AND ADMINISTRATION SECTIONS RELATED TO THE SPECIFIC PROCEDURES. HOWEVER, IT SHOULD BE UNDERSTOOD THAT THE INFORMATION IN THE GENERAL SECTIONS IS ALSO LIKELY TO APPLY TO ALL OF THESE SPECIFIC USES.

Hydration—With the possible exception of urography, patients should be fully hydrated prior to the following procedures.

EXCRETORY UROGRAPHY

Dehydration (fluid deprivation for 12 to 15 hours) improves urographic contrast especially at lower dosage level (see PRECAUTIONS—General). A preparatory laxative at bedtime to reduce gas and feces is often employed.

Diatrizoate salts are used in small, medium, and large dose urography. (See Dosage and Administration—EXCRETORY UROGRAPHY.) Visualization of the urinary tract can be achieved by either direct intravenous bolus injection, intravenous drip infusion, or sometimes by intramuscular or subcutaneous injections, or incidentally following intra-arterial procedure.

In infants less than 1 month only visualization of the urinary tract is delayed, therefore the number of roentgen exposures during the early part of the examination should be limited.

In patients with substantially impaired renal function and in patients with urinary tract obstruction, optimal visualization may be delayed for as long as 60 minutes or more. In such patients large doses may be required for adequate urograms.

For distribution and excretion of diatrizoates, see CLINICAL PHARMACOLOGY.

CONTRAINDICATION

Urography is contraindicated in patients with anuria.

PRECAUTIONS

See PRECAUTIONS—General. Some clinicians consider multiple myeloma a contraindication to excretory urography because of the great possibility of producing transient to fatal renal failure. Others believe that the risk of causing anuria is definite but small. If excretory urography is performed in the presence of multiple myeloma, dehydration should be avoided since it favors protein precipitation in renal tubules.

Although azotemia is not considered a contraindication, care is required in patients with advanced renal failure. The usual preparatory dehydration should be omitted, and urinary output should be observed for one to two days in these patients. Adequate visualization may be difficult or impossible to attain in patients with severely impaired renal and/or hepatic function. Use with extreme caution in patients with concomitant hepatorenal disease.

Preparatory Dehydration

Preparatory dehydration is dangerous in infants, young children, the elderly, and azotemic patients (especially those with polyuria, oliguria, diabetes, advanced vascular disease, or preexisting dehydration). The undesirable dehydration in these patients may be accentuated by the osmotic diuretic action of the medium.

Dehydration may improve image quality in patients with adequate renal function particularly if a low dose is used. Dehydration, however, will not improve contrast quality in patients with substantial renal insufficiencies and will increase risk of contrast induced renal damage. Dehydration in these patients is therefore contraindicated.

ADVERSE REACTIONS

See ADVERSE REACTIONS—General.

DOSAGE AND ADMINISTRATION

INTRAVENOUS DOSAGE

Adults. A dose of 30 mL of the 50 percent solution administered intravenously with or without compression produces diagnostic shadows in the majority of adults subjected to partial dehydration and to effective purgation. If the administration of 30 mL does not provide satisfactory visualization, this dose may be repeated in 15 to 30 minutes. In persons of slight build 20 mL may produce adequate shadows.

Larger doses ranging from 50 mL to 60 mL of the 50 percent solution may be used for routine excretory urography in adults. The increased dosage offers better and more complete visualization of the urinary tract. This technique requires neither compression nor dehydration and is more effective in obese patients. Adverse reactions to the larger dose are similar to those encountered with lower doses without an increase in incidence, severity, or type of reactions. Voiding cystourethrograms may be obtained when desired. For the best results and minimal side effects, it is advisable to inject the total amount of solution intravenously in one to three minutes.

Children. The dosage of the 50 percent solution for children under 6 months of age is 5 mL; for children 6 to 12 months of age, 6 mL to 8 mL; for children 1 to 2 years of age, 8 mL to 10 mL; for children 2 to 5 years of age, 10 mL to 12 mL; for children 5 to 7 years of age, 12 mL to 15 mL; for children 7 to 11 years of age, 15 mL to 18 mL, and for children 11 to 15 years of age, 18 mL to 20mL.

Subcutaneous or Intramuscular Urography

HYPAQUE sodium 50 percent may be used for excretory urography via intramuscular injection, undiluted or diluted; or subcutaneously diluted with equal quantities of sterile water for injection.

The intramuscular injection site generally used is the gluteal muscles in two separate, equal doses. Used subcutaneously the medium is generally injected in divided equal doses over each scapula.

In both locations the contrast medium is rapidly absorbed providing urograms beginning variously 5 to 10 minutes following intramuscular injection; subsequent exposures being made according to degree of pyelographic contrast.

Radiographs with subcutaneous injection are usually exposed at 10, 20, and 30 minutes. The urograms achieved with either methods will be almost equal to that following intravenous injection.

The usual intramuscular or subcutaneous (diluted) dose of HYPAQUE sodium 50 percent in adults and older children is about 20 mL to 30 mL. For infants and young children, the dose ranges from 5 mL to 16 mL.

Roentgenography

A plain film is often made prior to IVP. A nephrogram effect is available in 30 to 60 seconds. Its duration is dose dependent.

Urograms may be available as early as two minutes.However, urograms of optimal density are usually made at 5, 10, or 15 minutes following injection.

Ureteric films are usually made between 10 and 20 minutes, and cystograms at 30 minutes. In impaired renal function, delayed films may be required.

ANGIOGRAPHY

Angiography should be avoided whenever possible in patients with homocystinuria, because of the risk of inducing thrombosis and embolism.

CEREBRAL ANGIOGRAPHY

HYPAQUE sodium 50 percent may be administered for visualization of the cerebral vessels. In as much as cerebral angiography is a highly specialized procedure requiring the use of special techniques, it is recommended that HYPAQUE sodium 50 percent be used for this purpose only by persons skilled and experienced in carrying out the procedure.

CONTRAINDICATION

Carotid angiography during the progressive period of a stroke should be avoided, particularly on the left side because of the increased risk of cerebral complications.

PRECAUTIONS

See PRECAUTIONS—General. Patients in whom cerebral angiography is to be performed should be selected with care.

Although cerebral angiography has been considered contraindicated in patients who have recently experienced cerebral embolism or thrombosis (stroke syndrome), many experts now believe that the diagnostic value of the procedure, when employed early as an aid in locating lesions amenable to operation, outweighs any added risk to the patient. Furthermore, a small number of postangiographic fatalities have been reported, including progressive thrombosis already clinically evident before angiography, in which the procedure did not appear to play any direct role. Patients with severe cerebrovascular disease should be examined primarily by indirect methods of angiography.

In cerebral angiography, every precaution must be taken to prevent untoward reactions. Reactions may vary directly with the concentration of the substance, the amount used, the speed and frequency of injections, and the interval between injections.

In subarachnoid hemorrhage, angiography is expected to be hazardous. In migraine, the procedure can be hazardous because of ischemic complications, particularly if performed during or soon after an attack.

ADVERSE REACTIONS

See ADVERSE REACTIONS—General. With any contrast medium introduced into the cerebral vasculature, neurologic complications, including neuromuscular disorders, seizures, loss of consciousness, hemiplegia, unilateral dysesthesias, visual field defects, language disorders (aphasia), amnesia, and respiratory difficulties may occur, particularly when the extent of the intrinsic lesion is unknown. Such untoward reactions are for the most part temporary, although permanent visual field defects have been reported. Some investigators who are experienced in angiographic procedure emphasize the fact that they tend to occur after repeated injections or higher doses of the contrast medium. Other clinicians find that they occur most frequently in elderly patients. In as much as the procedure itself is attended by technical difficulties regardless of the risk the patient presents (eg, mechanical catheter obstruction of the vertebral artery can cause transient blindness), the more experienced the radiologic team, the fewer the complications of any degree that are apt to arise.

Amaurosis can occur following carotid or especially selective vertebral arteriography. It is almost always transitory (4 to 48 hours).

DOSAGE AND ADMINISTRATION

A dose of 8 mL to 12 mL injected at a rate not exceeding the normal flow in the carotid artery (about 5 mL per second) is suggested. The dose may be repeated as indicated; however, an increased risk attends each repeat injection. In the retrograde brachial or catheter method (aortic arch), a single injection of 35 mL to 50 mL is generally used. Children require a smaller dose in proportion to weight. Light anesthesia may be required in these procedures.

PERIPHERAL ANGIOGRAPHY

HYPAQUE sodium 50 percent may be administered for peripheral arteriography and for venography.

PRECAUTIONS

See PRECAUTIONS—General. Extreme caution is advised in considering peripheral arteriography in patients suspected of having thromboangiitis obliterans (Buerger’s disease) since any procedure (even insertion of a needle or catheter) may induce a severe arterial or venous spasm. Caution is also advisable in patients with severe ischemia associated with ascending infection.

ADVERSE REACTIONS

See ADVERSE REACTIONS—General. Soreness in extremities has also been reported.

Adverse reactions observed during peripheral arteriography may sometimes be due to arterial trauma during the procedure (ie, insertion of needle or catheter, subintimal injection, perforation) as well as to the hypertonicity or effect of the medium. Reported adverse reactions include transient arterial spasm, extravasation, hemorrhage, hematoma formation with tamponade, injury to nerves in close proximity to artery, thrombosis, dissecting aneurysm, arteriovenous fistula (eg, with accidental perforation of femoral artery and vein during the needing), and transient leg pain from contraction of calf muscles in femoral arteriography. Transient hypotension has been reported after intra-arterial (brachial) injection of the medium. Also, brachial plexus injury has been reported with axillary artery injections.

During venography in the presence of venous stasis, inflammatory changes and thrombosis may occur. Thrombosis is rare if the vein is irrigated following the injection.

DOSAGE AND ADMINISTRATION

Diagnostic arteriograms may be obtained with 25 mL to 35 mL of HYPAQUE sodium 50 percent introduced into the larger peripheral arteries by percutaneous or operative methods. Visualization of veins in the extremities may be accomplished with 15 mL to 40 mL.

AORTOGRAPHY

HYPAQUE sodium 50 percent may be administered intravenously or intra-arterially by accepted techniques to visualize the aorta and its major branches.

WARNINGS

Pheochromocytoma. Administration of angiographic media to patients known or suspected to have pheochromocytoma can cause dangerous changes in blood pressure. A minimum dose should be injected. The blood pressure should be carefully monitored and measures for controlling major fluctuations should be available.

During aortography by the translumbar technique, extreme care is advised to avoid inadvertent intrathecal injection since the injection of even small amounts (5 mL to 7 mL) of the contrast medium may cause convulsions, permanent sequelae, or fatality. Should the accident occur, the patient should be placed upright to confine the hyperbaric solution to a low level, anesthesia may be required to control convulsions, and if there is evidence of a large dose having been administered, a careful cerebrospinal fluid exchange-washout should be considered.

PRECAUTIONS

The presence of a vigorous pulsatile flow should be established before using a catheter or pressure injection technique. A small "pilot" dose (about 2 mL) should be administered to locate the exact site of needle or catheter tip to help prevent injection of the main dose into a branch of the aorta or intramurally. In the translumbar technique, severe pain during injection may indicate intramural placement and abdominal or back pain afterwards may indicate hemorrhage from the injection site. ollowing catheter procedures, gentle pressure hemostasis for 5 to 10 minutes is advised, followed by observation for 30 to 60 minutes and immobilization of the limb for several hours to prevent hemorrhage from the site of arterial puncture.

The care and experience with which the procedure is performed, the amount and type of medium used, the age and condition of the patient, and the premedication and anesthesia employed, influence the incidence and severity of reactions or complications that may be encountered. Since aortography is not without some danger, it should be employed only by persons experienced in the technique.

Repeated injections of the solution during a single study should be avoided whenever possible.

Under conditions of slowed aortic circulation there is an increased likelihood of aortography causing muscle spasm. Occasional serious neurologic complications, including paraplegia, have also been reported in patients with aortic-iliac or even femoral artery bed obstruction, abdominal compression, hypotension, hypertension, spinal anesthesia, injection of vasopressors to increase contrast, and low injection sites (L2-3). In these patients the concentration, dose, and number of repeat injections of the medium should be maintained at a minimum with appropriate intervals between injections. The position of the patient and catheter tip should be carefully evaluated.

Aortic Branches. Since serious neurologic complications, including quadriplegia, have occasionally been reported following spinal arteriography or selective injection of arterial trunks providing spinal artery branches (usually the thyrocervical, costocervical, subclavian, vertebral, bronchial, intercostal), great care is necessary to avoid entry of a large concentrated bolus of the medium. Thus, a "pilot" dose may establish correct position of the catheter tip. The concentration of the medium should not be over 50 percent. The carefully individualized dose is usually under 5 mL but preferably 3 mL to 4 mL and the number of repeat injections held to a minimum with appropriate intervals between injections. Pain or muscle spasm during the injection may require reevaluation of the procedure.

ADVERSE REACTIONS

The most common reaction to the medium is a mild burning sensation on injection. In addition to the reactions described in the general section, the following have been reported: mesenteric and intestinal necrosis, acute pancreatitis, renal shutdown (usually transitory), and neurologic complications following inadvertent injection of a large part of the aortic dose into a branch of the aorta. Entry of the large aortic dose into the renal artery can cause, even in the absence of symptoms, albuminuria, cylindruria, and hematuria, and an elevated BUN. Rapid and complete return of function usually follows. Also reported are coronary occlusion, hemorrhage from puncture site, arterial perforation by catheter or needle, thrombosis, embolism, and subintimal injection with aortic dissection by the medium.

DOSAGE AND ADMINISTRATION

The amount of each individual dose is a more important consideration than the total dosage used. Sufficient time should elapse between each injection to allow for subsidence of hemodynamic disturbances.

Retrograde (catheter) aortography—For adults and children, 0.5 mL to 1 mL per kg of bodyweight.

Intravenous aortography—For adults and children, 1 mL per kg of body weight.

Translumbar aortography—For adults, 10 mL to 30 mL. For children under 12 years, the dose is proportionate to age.

Selective renal arteriography—For adults and children over 14 years of age, 5 mL to 8 mL with repeat injections as indicated. For younger children, the dose is proportionate to age.

INTRAOSSEOUS VENOGRAPHY

The 50 percent solution may be injected directly into the bone marrow in the study of venous circulation of the bone and extraosseous tissue in the immediate drainage area.

A general anesthetic is sometimes necessary since the method is painful. Occasionally, extravasation of the contrast medium from the needle into the soft tissue may occur.

DOSAGE AND ADMINISTRATION

After aspiration of 4 mL of marrow, 10 mL to 20 mL of the medium are injected.

To visualize the pterygoid venous plexus, 5 mL to 8 mL of the contrast medium are injected into the medullary cavity of the mandible.

DIRECT CHOLANGIOGRAPHY

PRECAUTION

In the presence of acute pancreatitis, direct cholangiography, if necessary, should be employed with caution, injecting no more than 5 mL to 10 mL without undue pressure.

ADVERSE REACTION

Adverse reactions may often be attributed to injection pressure or excessive volume of the medium, resulting in overdistention. Such pressure may produce a sensation of epigastric fullness, followed by moderate pain in the back or right upper abdominal quadrant, which will subside when injection is stopped.

Hepatobiliary reflux of the medium may cause a pancholangitis or hepatitis which is usually transitory. Retrograde spread of the infection may produce liver abscess or septicemia. Pancreatic duct reflux may cause a transitory increase in serum amylase for a period of 6 to 18 hours without ill effects. Rarely it may cause pancreatitis.

DOSAGE AND ADMINISTRATION

The solution should be warmed to body temperature before administration. The injection is made slowly without undue pressure, taking great care to avoid introducing bubbles.

Operative—If no resistance is encountered, from 10 mL to 15 mL of a 25 percent to 50 percent solution is injected or instilled into the cystic duct or common bile duct, as indicated. In patients with obstructive jaundice, 40 mL to 50 mL of the medium may be injected directly into the gallbladder after aspiration of its contents.

Postexploratory or completion T tube cholangiography may also be performed after exploration of the common bile duct.

Postoperative—Delayed cholangiograms are usually made from the fifth to the tenth postoperative day prior to removal of the T tube.

In case of a dilated ductal tract, a larger volume (up to 100 mL) of radiopaque medium may be required for complete filling and visualization.

Percutaneous transhepatic cholangiography is recommended for carefully selected patients for the differential diagnosis of jaundice due to extrahepatic biliary obstruction or parenchymal disease. The procedure is only employed where oral or intravenous cholangiography and other procedures have failed to provide the necessary information. In obstructive cases, percutaneous transhepatic cholangiography is used to determine the cause and site of the obstruction to help plan surgery. The technique may also be of value in avoiding laparotomy in poor risk jaundice patients since failure to enter a duct suggest hepatocellular disease. Careful attention to technique is essential for the success and safety of the procedure. The procedure is usually performed under local anesthesia following analgesic premedication (eg, 100 mg meperidine intramuscularly).

CONTRAINDICATIONS

Percutaneous transhepatic cholangiography is contraindicated in patients with coagulation defects and prolonged prothrombin times until normal, or near normal, coagulation is achieved, eg, with vitamin K.

PRECAUTIONS

Percutaneous transhepatic cholangiography should only be attempted when compatible blood for potential transfusions is in readiness and emergency surgical measures are available. The patient should be carefully monitored for at least 24 hours to insure prompt detection of bile leakage and hemorrhage. Cholespastic premedication, as with morphine, should be avoided. Respiratory movements should be controlled during introduction of the needle.

ADVERSE REACTIONS

In percutaneous transhepatic cholangiography, some discomfort is common, but severe pain is nusual. Complications of the procedure are often serious and have been reported in four to six percent of patients. These reactions have included bile leakage and peritonitis, which are more likely to occur in patients with obstructions that cause unrelieved high biliary pressure. Bleeding (sometimes massive with exsanguination) may occur, especially in patients with clotting abnormalities. Blood-bile fistula, manifested by an early urogram (within 2 minutes), has been reported. Hypotension with fever and chills, as manifestations of septicemia, have occurred. Tension pneumothorax, cholangitis, and bacteremia have been reported.

DOSAGE AND ADMINISTRATION

As the needle is advanced or withdrawn, a bile duct may be located by frequent aspiration for bile or mucus into syringe filled with normal saline. As much bile as possible is aspirated. The usual dose of HYPAQUE sodium 50 percent is 20 mL to 40 mL but the range can be from 10 mL to 60 mL depending on degree of biliary dilatation present. The injection may be repeated for exposures in different planes. If a duct is not readily located by aspiration, entry may be established by injection of successive small doses of 1 mL to 2 mL of the medium under x-ray observation as the needle is withdrawn. If a duct is not located after three or four attempts, the procedure should be abandoned. Inability to enter a duct strongly suggests hepatocellular disease.

HYSTEROSALPINGOGRAPHY

Hysterosalpingography may be performed with either the 50 percent solution, or if a somewhat more viscous solution is preferred, diatrizoate meglumine and diatrizoate sodium, 90 percent.

CONTRAINDICATIONS

The procedure should not be performed during the menstrual period or when menstrual flow is imminent, nor should it be performed when infection is present in any portion of the genital tract, including the external genitalia. The procedure is also contraindicated for pregnant women or for those in whom pregnancy is suspected. Its use is not advised for six months after termination of pregnancy, or 30 days after conization or curettage.

PRECAUTION

In patients with carcinoma or in those in whom the condition is suspected, caution should be exercised to avoid possible spread of the lesion by the procedure.

ADVERSE REACTIONS

Cramping may occur during the injection and sometimes mild lower abdominal pain may be present for an hour or two afterwards. Even when the medium gains entrance into venous or lymphatic channels, systemic effects are rare. Generalized urticaria or slight transient hyperpyrexia, however, has been reported.

DOSAGE AND ADMINISTRATION

Preparation of the Patients

It is preferable to perform the procedure approximately 10 days after the patient’s menstrual period.

The patient should empty the bladder before the examination. An enema and vaginal douche are not essential but may be given one hour before the study. Premedication is not necessary.

Approximately 4 mL will suffice to fill a normal uterine cavity, with an additional 3 mL or 4 mL for the fallopian tubes. These amounts may vary depending on the nature of the disease.

SPLENOPORTOGRAPHY

INDICATION

Splenoportography is usually performed under mild preoperative sedation and under local anesthesia.

CONTRAINDICATIONS

Splenoportography should not be performed on any patient for whom splenectomy is contraindicated, since complications of the procedure at times make splenectomy necessary. Other contraindications include prolonged prothrombin time or other coagulation defects, significant thrombocytopenia, and any condition which may increase the possibility of rupture of the spleen.

Precautions

Prior gastrointestinal x-ray examination should include particular attention to the lower esophageal area. A hematologic survey, including prothrombin time and platelet count, should be performed. To minimize risk of bleeding, manipulation during or after entry of the needle should be avoided. Caution is advised in patients whose spleen has recently become tender and palpable.

Following splenoportography, the patient should lie on his left side for several hours and should be closely observed for 24 hours for signs of internal bleeding.

Adverse Reactions

Internal bleeding is the most common serious complication of splenoportography. Although leakage of up to 300 mL of blood is apparently not uncommon, sometimes blood transfusions and rarely, splenectomy, may be required to control hemorrhage. Peritoneal extravasation may cause transient diaphragmatic irritation or mild to moderate transient pain which may sometimes be referred to the shoulder, the periumbilical region, or other areas. Because of the proximity of the pleural cavity, accidental pneumothorax has been known to occur. Inadvertent injection of the medium into other nearby structures is not likely to cause untoward consequences.

Dosage And Administration

A preliminary small "pilot" dose is injected to confirm splenic entry, followed usually by rapid injection of 20 mL to 25 mL of HYPAQUE sodium 50 percent. Rapid serial exposures are started with the injection of the dose and continued until contrast is observed in the entire portal system.

CONTRAST ENHANCEMENT OF COMPUTED TOMOGRAPHIC HEAD IMAGING

Precautions

Metastatic Brain Lesions: Large doses of contrast media should be avoided in patients with suspected metastatic brain lesions. Intravenous administration of large doses to these patients is more likely to result in convulsions; however, these occurrences are rare. This has been attributed to tissue accumulation of the medium in the presence of blood brain barrier disruption caused by disease. Appropriate measures for seizure management should be immediately available.

Convulsion: (See PRECAUTIONS—General).

Dosage And Administration

Bolus intravenous injection of 50 mL to 100 mL, or up to 150 mL by infusion. The rate of injection and the timing of scans will depend principally on the expected nature of the pathology. Dosage in children is proportional to adults, based on weight.

HOW SUPPLIED

Vials of 50 mL, rubber stoppered, box of 25 (NDC 0407-0766-04).

Protect from light. Store at 15°C to 30°C (59° F to 86°F).

Distributed by Amersham Health Inc.
Princeton, NJ 08540

Printed in USA

HNC-7F